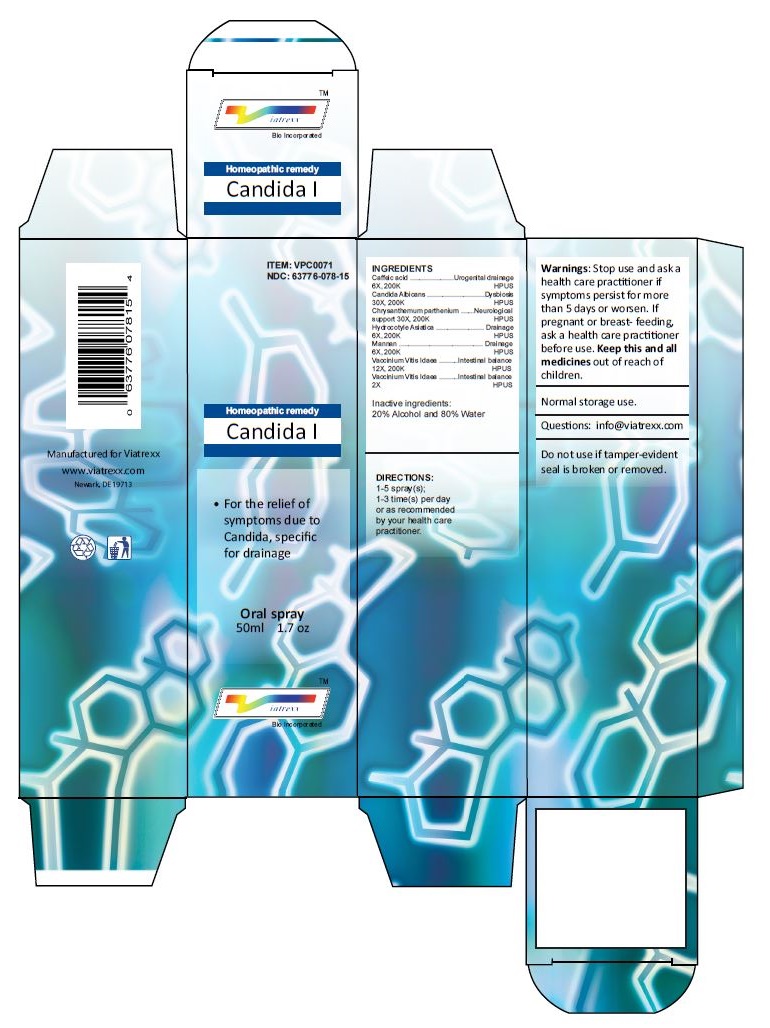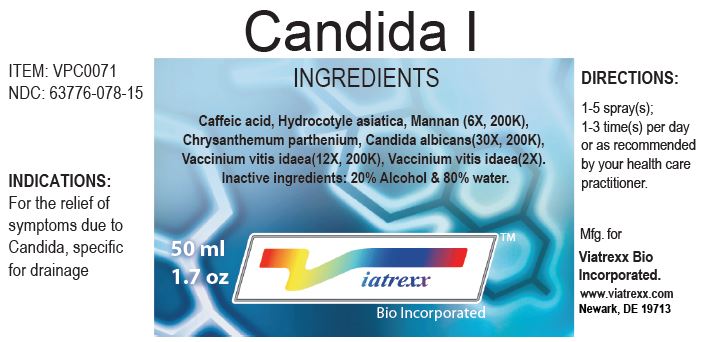 DRUG LABEL: Candida I
NDC: 63776-078 | Form: SPRAY
Manufacturer: VIATREXX BIO INCORPORATED
Category: homeopathic | Type: HUMAN OTC DRUG LABEL
Date: 20221130

ACTIVE INGREDIENTS: CAFFEIC ACID 200 [kp_C]/1 mL; CANDIDA ALBICANS 200 [kp_C]/1 mL; TANACETUM PARTHENIUM 200 [kp_C]/1 mL; CENTELLA ASIATICA 200 [kp_C]/1 mL; YEAST MANNAN 200 [kp_C]/1 mL; VACCINIUM VITIS-IDAEA LEAF 200 [kp_C]/1 mL
INACTIVE INGREDIENTS: ALCOHOL; WATER

Candida I

Active Ingredients

Caffeic acid 6X 200K, Candida Albicans 30X 200K, Chrysanthemum parthenium 30X, 200K, Hydrocotyle Asiatica 6X 200K, Mannan 6X 200K, Vaccinium Vitis Idaea 12X 200K, Vaccinium Vitis Idaea 2X

Purpose:

Caffeic acid | Urogenital drainage
Candida Albicans | Dysbiosis
Chrysanthemum parthenium | Neurological support
Hydrocotyle Asiatica | Drainage
Mannan | Drainage
Vaccinium Vitis Idaea | Intestinal balance
Vaccinium Vitis Idaea | Intestinal balance

Uses

For the relief of symptoms due to Candida, specific for drainage

Warnings

Stop use and ask a health care practitioner if symptoms persist for more than 5 days or worsen. If pregnant or breastfeeding, ask a health care practitioner before use.

Dosage

1-5 spray(s); 1-3 time(s) per day or as recommended by your health care practitioner.

KEEP OUT OF REACH OF CHILDREN

Keep this and all medicines out of reach of children.

Other Ingredients

Alcohol and Water

Other Information

Normal storage use.
Do not use if tamper-evident seal is broken or removed.

Questions

info@viatrexx.com

Principal Display Panel

ITEM: VPC0071
NDC 63776-078-15
Homeopathic remedy
Candida I
• For the relief of symptoms due to Candida, specific for drainage
Oral spray
50ml 1.7 oz
Viatrexx™ Bio Incorporated
Manufactured by Viatrexx
www.viatrexx.com
Newark, DE 19713

Candida I
50 mL
1.7 oz
Viatrexx™ Bio Incorporated
ITEM: VPC0071
NDC: 63776-078-15
INDICATIONS:
For the relief of symptoms due to Candida, specific for drainage
DIRECTIONS:
1-5 spray(s); 1-3 time(s) per day or as recommended by your health care practitioner.
Mfg. for
Viatrexx Bio Incorporated.
www.viatrexx.com
Newark, DE 19713